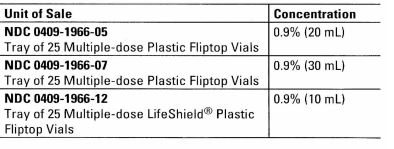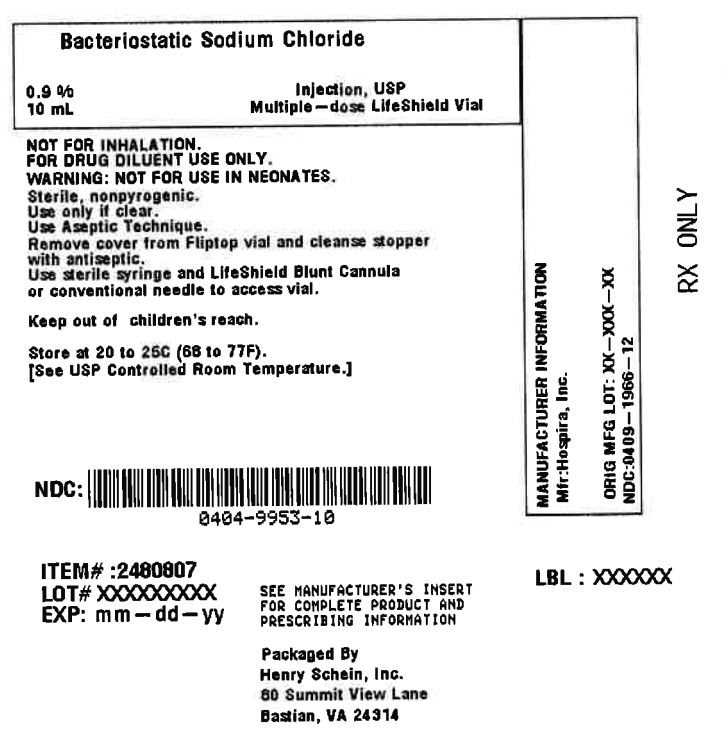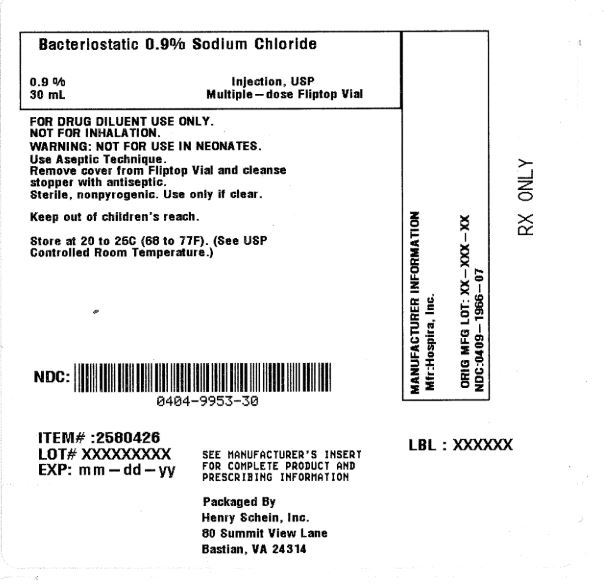 DRUG LABEL: Bacteriostatic Sodium Chloride
NDC: 0404-9953 | Form: INJECTION, SOLUTION
Manufacturer: Henry Schein, Inc.
Category: prescription | Type: HUMAN PRESCRIPTION DRUG LABEL
Date: 20251107

ACTIVE INGREDIENTS: Sodium Chloride 9 mg/1 mL

Bacteriostatic 0.9% Sodium Chloride 0.9% Injection, USP 30 mL Multi Dose Vial

DESCRIPTION

This preparation is designed for parenteral use only after addition of drugs that require dilution or must be dissolved in an aqueous vehicle prior to injection.

Bacteriostatic 0.9% Sodium Chloride Injection, USP is a sterile, nonpyrogenic, isotonic solution of sodium chloride in water for injection. Each milliliter (mL) contains sodium chloride 9 mg and 0.9% (9 mg/mL) benzyl alcohol added as a bacteriostatic preservative. May contain hydrochloric acid for pH adjustment. It is supplied in a multiple-dose container from which repeated withdrawals may be made to dilute or dissolve drugs for medication. The pH is 5.0 (4.5 to 7.0).

Sodium Chloride, USP is chemically designated NaCl, a white crystalline powder freely soluble in water.

The semi-rigid vial is fabricated from a specially formulated polyolefin. It is a copolymer of ethylene and propylene. The safety of the plastic has been confirmed by tests in animals according to USP biological standards for plastic containers. The container requires no vapor barrier to maintain the proper drug concentration.

CLINICAL PHARMACOLOGY

Sodium chloride in water dissociates to provide sodium (Na^+) and chloride (Cl^−) ions. These ions are normal constituents of the body fluids (principally extracellular) and are essential for maintaining electrolyte balance.

The distribution and excretion of sodium (Na^+) and chloride (Cl^−) are largely under the control of the kidney which maintains a balance between intake and output.

The small volume of fluid and amount of sodium chloride provided by Bacteriostatic 0.9% Sodium Chloride Injection, USP, when used only as a vehicle for parenteral injection of drugs, is unlikely to exert a significant effect on fluid and electrolyte balance except possibly in neonates and very small infants.

Water is an essential constituent of all body tissues and accounts for approximately 70% of total body weight. Average normal adult daily requirement ranges from two to three liters (1.0 to 1.5 liters each for insensible water loss by perspiration and urine production).

Water balance is maintained by various regulatory mechanisms. Water distribution depends primarily on the concentration of electrolytes in the body compartments and sodium (Na^+) plays a major role in maintaining physiologic equilibrium.

INDICATIONS AND USAGE

This parenteral preparation is indicated only for diluting or dissolving drugs for intravenous, intramuscular or subcutaneous injection, according to instructions of the manufacturer of the drug to be administered.

CONTRAINDICATIONS

Due to the potential toxicity of benzyl alcohol in neonates, solutions containing benzyl alcohol must not be used in this patient population.

Parenteral preparations with benzyl alcohol should not be used for fluid or sodium chloride replacement.

Parenteral preparations containing benzyl alcohol should not be used in epidural or spinal anesthetic procedures.

WARNINGS

Benzyl alcohol, a preservative in Bacteriostatic Sodium Chloride Injection, USP has been associated with toxicity in neonates. Data are unavailable on the toxicity of other preservatives in this age group. Preservative-free Sodium Chloride Injection should be used for flushing intravascular catheters. Where a sodium chloride solution is required for preparing or diluting medications for use in neonates, only preservative-free Sodium Chloride Injection should be used.

PRECAUTIONS

Consult the manufacturer's instructions for choice of vehicle, appropriate dilution or volume for dissolving the drugs to be injected, including the route and rate of injection.

Inspect reconstituted (diluted or dissolved) drugs for clarity (if soluble) and freedom from unexpected precipitation or discoloration prior to administration.

Pregnancy: Animal reproduction studies have not been conducted with Bacteriostatic 0.9% Sodium Chloride Injection, USP. It is also not known whether Bacteriostatic 0.9% Sodium Chloride Injection containing additives can cause fetal harm when administered to a pregnant woman or can affect reproduction capacity. Bacteriostatic 0.9% Sodium Chloride Injection containing additives should be given to a pregnant woman only if clearly needed.

Pediatric Use

The safety and effectiveness in the pediatric population are based on the similarity of the clinical conditions of the pediatric and adult populations. However, due to potential toxicity of benzyl alcohol in neonates, solutions containing benzyl alcohol are contraindicated in this patient population.

Drug Interactions

Some drugs for injection may be incompatible in a given vehicle, or when combined in the same vehicle or in a vehicle containing benzyl alcohol. Consult with pharmacist, if available.

Use aseptic technique for single or multiple entry and withdrawal from all containers.

When diluting or dissolving drugs, mix thoroughly and use promptly.

Do not store reconstituted solutions of drugs for injection unless otherwise directed by the manufacturer of the solute.

Do not use unless the solution is clear and seal intact.

ADVERSE REACTIONS

Reactions which may occur because of this solution, added drugs or the technique of reconstitution or administration include febrile response, local tenderness, abscess, tissue necrosis or infection at the site of injection, venous thrombosis or phlebitis extending from the site of injection and extravasation.

If an adverse reaction does occur, discontinue the infusion, evaluate the patient, institute appropriate countermeasures, and if possible, retrieve and save the remainder of the unused vehicle for examination.

Although adverse reactions to intravenous, intramuscular or subcutaneous injection of 0.9% benzyl alcohol are not known to occur in man, experimental studies of small volume parenteral preparations containing 0.9% benzyl alcohol in several species of animals have indicated that an estimated intravenous dose up to 30 mL may be safely given to an adult without toxic effects. Administration of an estimated 9 mL to a 6 kg neonate or infant is potentially capable of producing blood pressure changes.

OVERDOSAGE

Use only as a diluent or solvent. This parenteral preparation is unlikely to pose a threat of sodium chloride or fluid overload except possibly in neonates and very small infants. In the event these should occur, re-evaluate the patient and institute appropriate corrective measures. See PRECAUTIONS and ADVERSE REACTIONS.

DOSAGE AND ADMINISTRATION

The volume of the preparation to be used for diluting or dissolving any drug for injection, is dependent on the vehicle concentration, dose and route of administration as recommended by the manufacturer.

Parenteral drug products should be inspected visually for particulate matter and discoloration prior to administration, whenever solution and container permit. See PRECAUTIONS.

HOW SUPPLIED

Bacteriostatic 0.9% Sodium Chloride Injection, USP is supplied as:

Store at 20 to 25°C (68 to 77°F). [See USP Controlled Room Temperature.]

LifeShield® is the trademark of ICU Medical, Inc. and is used under license.

Distributed by Hospira, Inc., Lake Forest IL 60045 USA
LAB-1096-3.0
Revised: 02/2019

Product repackaged by: Henry Schein, Inc., Bastian, VA 24314
From Original Manufacturer/Distributor's NDC and Unit of Sale | To Henry Schein Repackaged Product NDC and Unit of Sale | Total Strength/Total Volume (Concentration) per unit
NDC 0409-1966-12; Tray of 25 Multiple-Dose Lifeshield® Plastic Fliptop Vials | NDC 0404-9953-10; 1 Multiple-Dose Lifeshield® Plastic Fliptop Vial in a bag (Vial bears NDC 0409-1966-06) | 0.9% (10 mL)
NDC 0409-1966-07; Tray of 25 Multiple-Dose Plastic Fliptop Vials | NDC 0404-9953-30; 1 Multiple-Dose Plastic Fliptop Vial in a bag (Vial bears NDC 0409-1966-02) | 0.9% (30 mL)